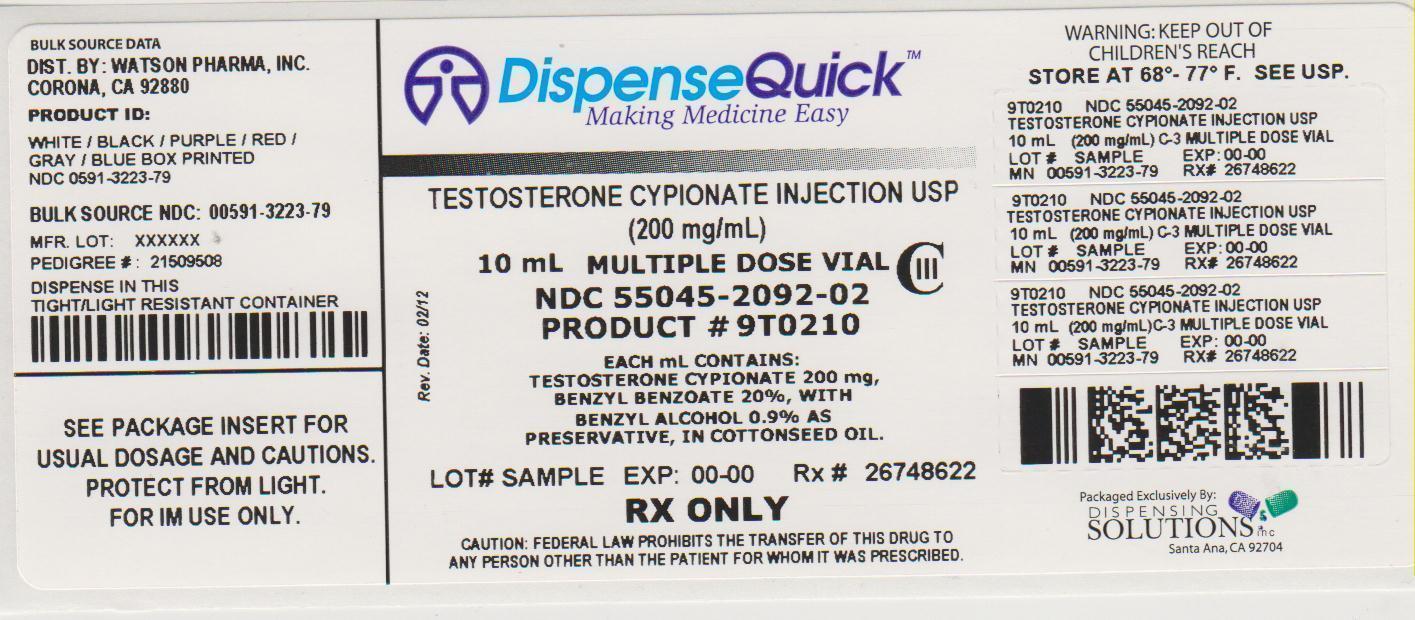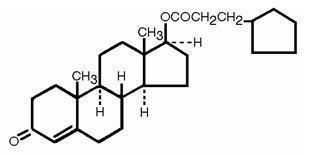 DRUG LABEL: Testosterone Cypionate
NDC: 55045-2092 | Form: INJECTION, SOLUTION
Manufacturer: Dispensing Solutions, Inc.
Category: prescription | Type: HUMAN PRESCRIPTION DRUG LABEL
Date: 20121002
DEA Schedule: CIII

ACTIVE INGREDIENTS: TESTOSTERONE CYPIONATE 200 mg/1 mL
INACTIVE INGREDIENTS: BENZYL BENZOATE 223.6 mg/1 mL; BENZYL ALCOHOL 9.9 mg/1 mL; COTTONSEED OIL

TESTOSTERONE CYPIONATE INJECTION USP
FOR INTRAMUSCULAR USE ONLY C-III
Rx only

DESCRIPTION

Testosterone Cypionate Injection for intramuscular injection, contains testosterone cypionate which is the oil-soluble 17 (beta)- cyclopentylpropionate ester of the androgenic hormone testosterone.

Testosterone cypionate is a white or creamy white crystalline powder, odorless or nearly so and stable in air. It is insoluble in water, freely soluble in alcohol, chloroform, dioxane, ether, and soluble in vegetable oils.

The chemical name for testosterone cypionate is androst-4-en-3-one,17-(3-cyclopentyl-1-oxopropoxy)-, (17β)-. Its molecular formula is C27H40O3 and the molecular weight 412.61.

The structural formula is represented below:

Each mL contains: Testosterone Cypionate 200 mg, Benzyl Benzoate 20%, with Benzyl Alcohol 0.9% as preservative in Cottonseed Oil q.s.

CLINICAL PHARMACOLOGY

Endogenous androgens are responsible for normal growth and development of the male sex organs and for maintenance of secondary sex characteristics. These effects include growth and maturation of prostate, seminal vesicles, penis, and scrotum; development of male hair distribution, such as beard, pubic, chest and axillary hair; laryngeal enlargement, vocal chord thickening, and alterations in body musculature and fat distribution. Drugs in this class also cause retention of nitrogen, sodium, potassium, and phosphorus, and decreased urinary excretion of calcium. Androgens have been reported to increase protein anabolism and decrease protein catabolism. Nitrogen balance is improved only when there is sufficient intake of calories and protein.

Androgens are responsible for the growth spurt of adolescence and for eventual termination of linear growth, brought about by fusion of the epiphyseal growth centers. In children, exogenous androgens accelerate linear growth rates, but may cause disproportionate advancement in bone maturation. Use over long periods may result in fusion of the epiphyseal growth centers and termination of the growth process. Androgens have been reported to stimulate production of red blood cells by enhancing production of erythropoietic stimulation factor.

During exogenous administration of androgens, endogenous testosterone release is inhibited through feedback inhibition of pituitary luteinizing hormone (LH). At large doses of exogenous androgens, spermatogenesis may also be suppressed through feedback inhibition of pituitary follicle stimulating hormone (FSH).

There is a lack of substantial evidence that androgens are effective in fractures, surgery, convalescence, and functional uterine bleeding.

Pharmacokinetics

Testosterone esters are less polar than free testosterone. Testosterone esters in oil injected intramuscularly are absorbed slowly from the lipid phase; thus, testosterone cypionate can be given at intervals of two to four weeks.

Testosterone in plasma is 98 percent bound to a specific testosterone-estradiol binding globulin, and about 2 percent is free. Generally, the amount of this sex-hormone binding globulin in the plasma will determine the distribution of testosterone between free and bound forms, and the free testosterone concentration will determine its half-life.

About 90 percent of a dose of testosterone is excreted in the urine as glucuronic and sulfuric acid conjugates of testosterone and its metabolites; about 6 percent of a dose is excreted in the feces, mostly in the unconjugated form. Inactivation of testosterone occurs primarily in the liver. Testosterone is metabolized to various 17-keto steroids through two different pathways.

The half-life of testosterone cypionate when injected intramuscularly is approximately eight days.

In many tissues the activity of testosterone appears to depend on reduction to dihydrotestosterone, which binds to cytosol receptor proteins. The steroid-receptor complex is transported to the nucleus where it initiates transcription events and cellular changes related to androgen action.

INDICATIONS AND USAGE

Testosterone Cypionate Injection is indicated for replacement therapy in the male in conditions associated with symptoms of deficiency or absence of endogenous testosterone.

1. Primary hypogonadism (congenital or acquired)-testicular failure due to cryptorchidism, bilateral torsion, orchitis, vanishing testis syndrome; or orchidectomy.
2. Hypogonadotropic hypogonadism (congenital or acquired)-idiopathic gonadotropin or LHRH deficiency, or pituitary-hypothalamic injury from tumors, trauma, or radiation.

CONTRAINDICATIONS

1. Known hypersensitivity to the drug
2. Males with carcinoma of the breast
3. Males with known or suspected carcinoma of the prostate gland
4. Women who are or who may become pregnant
5. Patients with serious cardiac, hepatic or renal disease

WARNINGS

Hypercalcemia may occur in immobilized patients. If this occurs, the drug should be discontinued.

Prolonged use of high doses of androgens (principally the 17-α alkyl-androgens) has been associated with development of hepatic adenomas, hepatocellular carcinoma, and peliosis hepatis – all potentially life-threatening complications.

Geriatric patients treated with androgens may be at an increased risk of developing prostatic hypertrophy and prostatic carcinoma although conclusive evidence to support this concept is lacking.

Edema, with or without congestive heart failure, may be a serious complication in patients with pre-existing cardiac, renal or hepatic disease.

Gynecomastia may develop and occasionally persists in patients being treated for hypogonadism.

This product contains benzyl alcohol. Benzyl alcohol has been reported to be associated with a fatal “Gasping Syndrome” in premature infants.

Androgen therapy should be used cautiously in healthy males with delayed puberty. The effect on bone maturation should be monitored by assessing bone age of the wrist and hand every 6 months. In children, androgen treatment may accelerate bone maturation without producing compensatory gain in linear growth. This adverse effect may result in compromised adult stature. The younger the child the greater the risk of compromising final mature height.

This drug has not been shown to be safe and effective for the enhancement of athletic performance. Because of the potential risk of serious adverse health effects, this drug should not be used for such purpose.

PRECAUTIONS

General

Patients with benign prostatic hypertrophy may develop acute urethral obstruction. Priapism or excessive sexual stimulation may develop. Oligospermia may occur after prolonged administration of excessive dosage. If any of these effects appear, the androgen should be stopped and if restarted, a lower dosage should be utilized.

Testosterone cypionate should not be used interchangeably with testosterone propionate because of differences in duration of action.

Testosterone cypionate is not for intravenous use.

Information for Patients

Patients should be instructed to report any of the following: nausea, vomiting, changes in skin color, ankle swelling, too frequent or persistent erections of the penis.

Laboratory Tests

Hemoglobin and hematocrit levels (to detect polycythemia) should be checked periodically in patients receiving long-term androgen administration.

Serum cholesterol may increase during androgen therapy.

Drug Interactions

Androgens may increase sensitivity to oral anticoagulants. Dosage of the anticoagulant may require reduction in order to maintain satisfactory therapeutic hypoprothrombinemia.

Concurrent administration of oxyphenbutazone and androgens may result in elevated serum levels of oxyphenbutazone.

In diabetic patients, the metabolic effects of androgens may decrease blood glucose and, therefore, insulin requirements.

Drug/Laboratory Test Interferences

Androgens may decrease levels of thyroxine-binding globulin, resulting in decreased total T4 serum levels and increased resin uptake of T3 and T4. Free thyroid hormone levels remain unchanged, however, and there is no clinical evidence of thyroid dysfunction.

Carcinogenesis

Animal Data

Testosterone has been tested by subcutaneous injection and implantation in mice and rats. The implant induced cervical-uterine tumors in mice, which metastasized in some cases. There is suggestive evidence that injection of testosterone into some strains of female mice increases their susceptibility to hepatoma. Testosterone is also known to increase the number of tumors and decrease the degree of differentiation of chemically-induced carcinomas of the liver in rats.

Human Data

There are rare reports of hepatocellular carcinoma in patients receiving long-term therapy with androgens in high doses. Withdrawal of the drugs did not lead to regression of the tumors in all cases.

Geriatric patients treated with androgens may be at an increased risk of developing prostatic hypertrophy and prostatic carcinoma although conclusive evidence to support this concept is lacking.

Pregnancy

Teratogenic Effects

Pregnancy Category X (SeeCONTRAINDICATIONS).

Nursing Mothers

Testosterone Cypionate Injection is not recommended for use in nursing mothers.

Pediatric Use

Safety and effectiveness in pediatric patients below the age of 12 years have not been established.

ADVERSE REACTIONS

The following adverse reactions in the male have occurred with some androgens:

Endocrine and Urogenital

Gynecomastia and excessive frequency and duration of penile erections. Oligospermia may occur at high dosages.

Skin and Appendages

Hirsutism, male pattern of baldness, seborrhea, and acne.

Fluid and Electrolyte Disturbances

Retention of sodium, chloride, water, potassium, calcium, and inorganic phosphates.

Gastrointestinal

Nausea, cholestatic jaundice, alterations in liver function tests, rarely hepatocellular neoplasms and peliosis hepatis (SeeWARNINGS).

Hematologic

Suppression of clotting factors II, V, VII, and X, bleeding in patients on concomitant anticoagulant therapy, and polycythemia.

Nervous System

Increased or decreased libido, headache, anxiety, depression, and generalized paresthesia.

Allergic

Hypersensitivity, including skin manifestations and anaphylactoid reactions.

Miscellaneous

Inflammation and pain at the site of intramuscular injection.

DRUG ABUSE AND DEPENDENCE

Controlled Substance Class: Testosterone is a controlled substance under the Anabolic Steroids Control Act, and Testosterone Cypionate Injection has been assigned to Schedule III.

OVERDOSAGE

There have been no reports of acute overdosage with the androgens.

DOSAGE AND ADMINISTRATION

Testosterone Cypionate Injection is for intramuscular use only. It should not be given intravenously. Intramuscular injections should be given deep in the gluteal muscle.

The suggested dosage for Testosterone Cypionate Injection varies depending on the age, sex, and diagnosis of the individual patient. Dosage is adjusted according to the patient’s response and the appearance of adverse reactions.

Various dosage regimens have been used to induce pubertal changes in hypogonadal males; some experts have advocated lower dosages initially, gradually increasing the dose as puberty progresses, with or without a decrease to maintenance levels. Other experts emphasize that higher dosages are needed to induce pubertal changes and lower dosages can be used for maintenance after puberty. The chronological and skeletal ages must be taken into consideration, both in determining the initial dose and in adjusting the dose.

For replacement in the hypogonadal male, 50-400 mg should be administered every two to four weeks.

Parenteral drug products should be inspected visually for particulate matter and discoloration prior to administration, whenever solution and container permit. Warming and shaking the vial should redissolve any crystals that may have formed during storage at temperatures lower than recommended.

HOW SUPPLIED

Testosterone Cypionate Injection USP, 200 mg/mL is available in:
10 mL multiple dose vials, individually boxed.

Store at 20°-25°C (68°-77°F) [See USP Controlled Room Temperature].

PROTECT FROM LIGHT.

Literature revised: July 2010
Product No.: 0256-10

Manufactured by:
Hikma Farmaceutica (Portugal)
S.A. 2705-906 Terrugem SNT, Portugal
Distributed by:
Watson Pharma, Inc.
Corona, CA 92880 USA

PIN230-WAT/1

Package Label

NDC 55045-2092-02
10 mL Multiple Dose Vial
Testosterone Cypionate Injection USP (200 mg/mL)
FOR INTRAMUSCULAR USE ONLY

Rx only
Sterile
Each mL contains:Testosterone Cypionate 200 mg,
Benzyl Benzoate 20%, with
Benzyl Alcohol 0.9% as
preservative, in Cottonseed Oil.
Usual adult dosage:See package insert.

Store at 20°-25°C (68°-77°F)
[See USP Controlled Room Temperature].

PROTECT FROM LIGHT.

Manufactured by:
Hikma Farmaceutica (Portugal)S.A. 2705-906 Terrugem SNT
Portugal
Distributed by:
Watson Pharma, Inc.
Corona, CA 92880 USA

Repackaged by:
Dispensing Solutions, Inc.
Santa Ana, CA 92704 USA